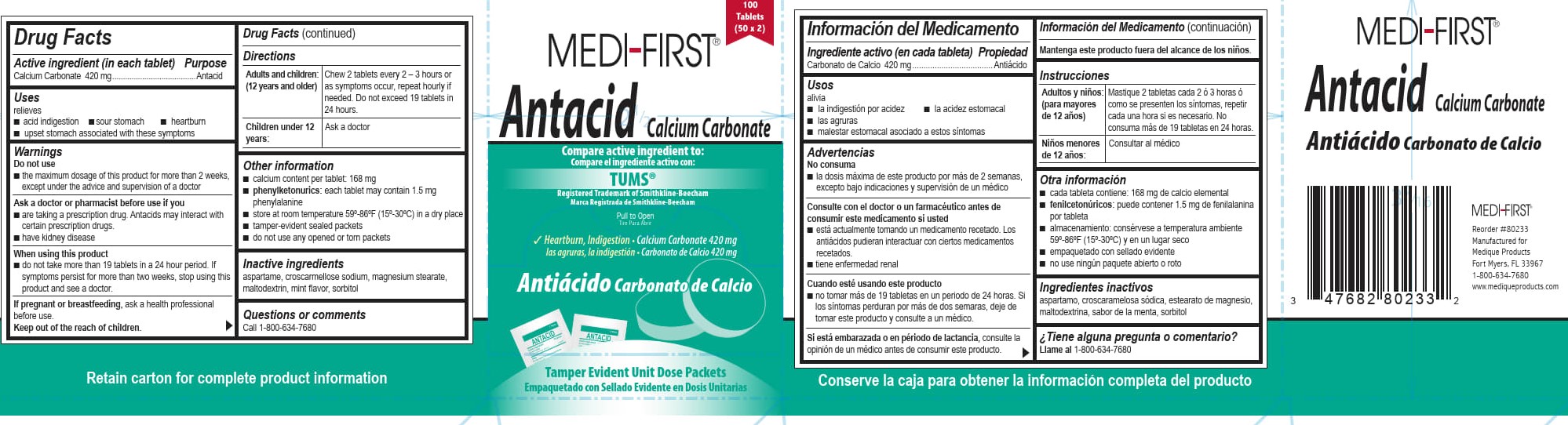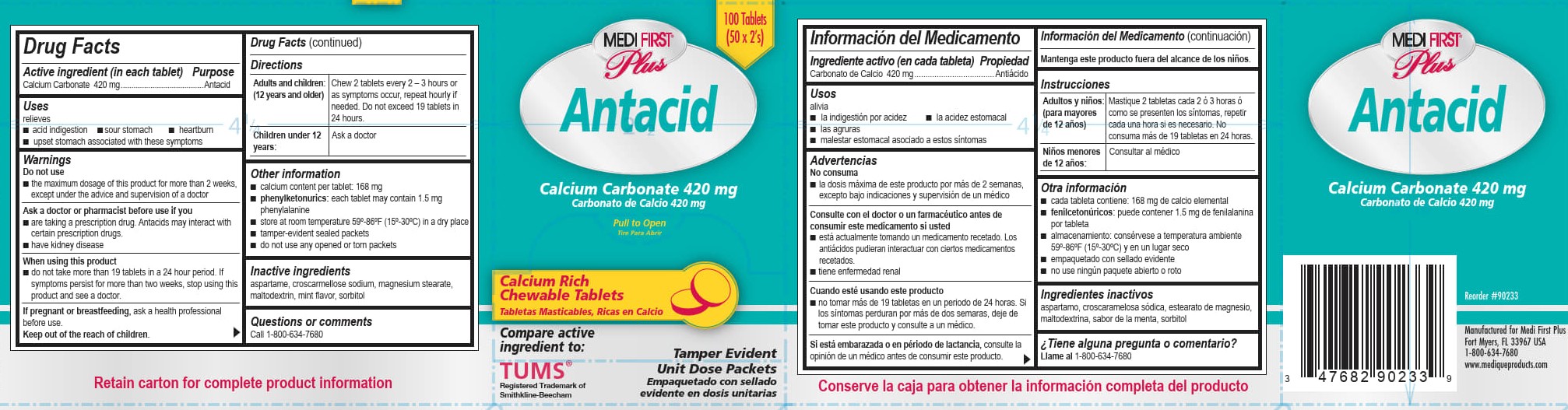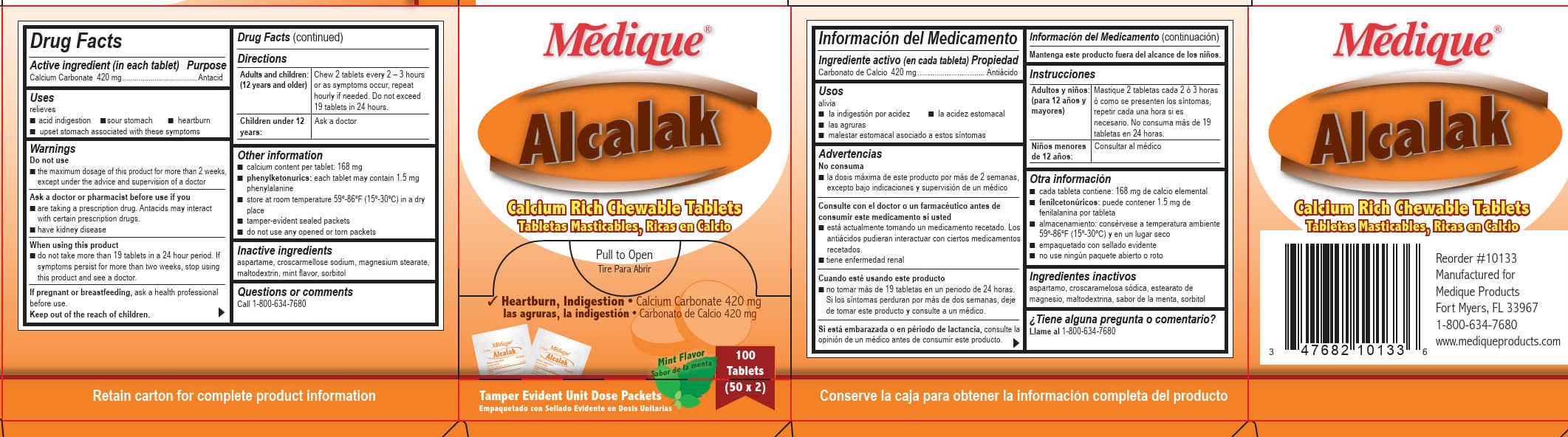 DRUG LABEL: Medique Alcalak
NDC: 47682-201 | Form: TABLET, CHEWABLE
Manufacturer: Unifirst First Aid Corporation
Category: otc | Type: HUMAN OTC DRUG LABEL
Date: 20250908

ACTIVE INGREDIENTS: CALCIUM CARBONATE 420 mg/1 1
INACTIVE INGREDIENTS: ASPARTAME; CROSCARMELLOSE SODIUM; MAGNESIUM STEARATE; MALTODEXTRIN; SORBITOL

Unifirst First Aid Antacid

Drug Facts

Active ingredient (in each tablet)

Calcium Carbonate 420 mg

Purpose

Antacid

Uses

relieves

- acid indigestion
- sour stomach
- heartburn
- upset stomach associated with these symptoms

Warnings

Do not use

■ the maximum dosage of this product for more than 2 weeks except under the advice and supervision of a

doctor

Ask a doctor or pharmacists before use if you

■ are taking a prescription drug. Antacids may interact with certain prescription drugs.

■ have kidney disease

When using this product

- do not ake more than 19 tablets in a 24 hour period. If symptoms persist for more than two weeks, stop using this product and see a doctor.

PREGNANCY OR BREAST FEEDING

If pregnant or breast feeding, ask a health professional before use.

Keep out of the reach of children.

Directions

Adults and children: (12 years and older) Chew 2 tablets every 2 - 3 hours or as symptoms occur, repeat hourly if needed. Do not exceed 19 tablets in 24 hours.

Children under 12 years: Ask a doctor

Other information

- calcium content per tablet: 168 mg
- phenylketonurics: each tablet may contain 1.5 mg phenylalanine
- store at room temperature 59-86°F (15-30°C) in a dry place
- tamper-evident sealed packets
- do not use any opened or torn packets

Inactive ingredients

aspartame*, croscarmellose sodium*, gum acacia*, magnesium stearate, maltodextrin, mint flavor, sorbitol*, sucrose*

*may contain

Questions or comments? Call 1-800-634-7680

Medique Alcalak

Medique ®

Alcalak

Calcium Rich Chewable Tablets

Tabletas Masticables, Ricas en Calcio

Pull to Open

Tire Para Abrir

Heartburn, Indigestion • Calcium Carbonate 420 mg

las agruras, la indigestion • Carbonato de Calcio 420 mg

Mint Flavor

200

Tablets
(100 x 2)

Tamper Evident Unit Dose Packets

Empaquetado con Sellado Evidente en Dosis Unitarias

Medi-First Antacid Label

100
Tablets
(50 x 2)

MEDI-FIRST ®

Antacid Calcium Carbonate

Compare active ingredient to:

Compare el ingrediente activo con:

Tums ®

Registered Trademark of Smithkline-Beecham

Marca Registrada de Smithkline-Beecham

Pull to Open

Tire Para Abrir

Heartburn, Indigestion • Calcium Carbonate 420mg

las agruras, la indigestion • Antiacido Carbonato de Calcio 420mg

Antiacido Carbonato de Calico

Tamper Evident Unit Dose Packets

Empaquetado con Sellado Evidente en Dosis Unitarias

Medi-First Plus Antacid Label

100
Tablets
(50 x 2)

MEDI-FIRST®

Plus

Antacid

Calcium Carbonate 420 mg

Carbonato de Calcio 420mg

Pull to Open

Tire Para Abrir

Calcium Rich

Chewable Tablets

Tabletas Masticables, Ricas en Calcio

Compare active

ingredient to:

Tums ®

Registered Trademark of Smithkline-Beecham

Tamper Evident

Unit Dose Packets

Empaquetado con Sellado

Evidente en Dosis Unitarias